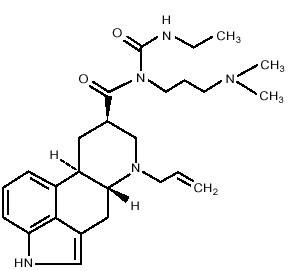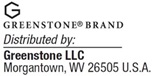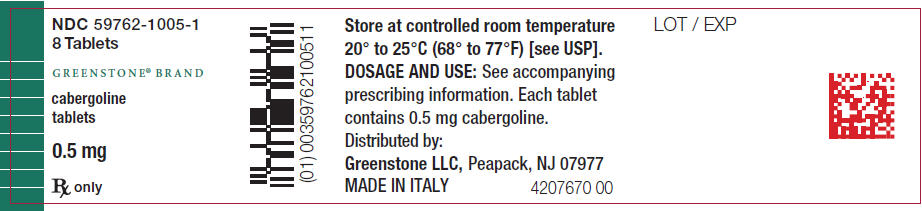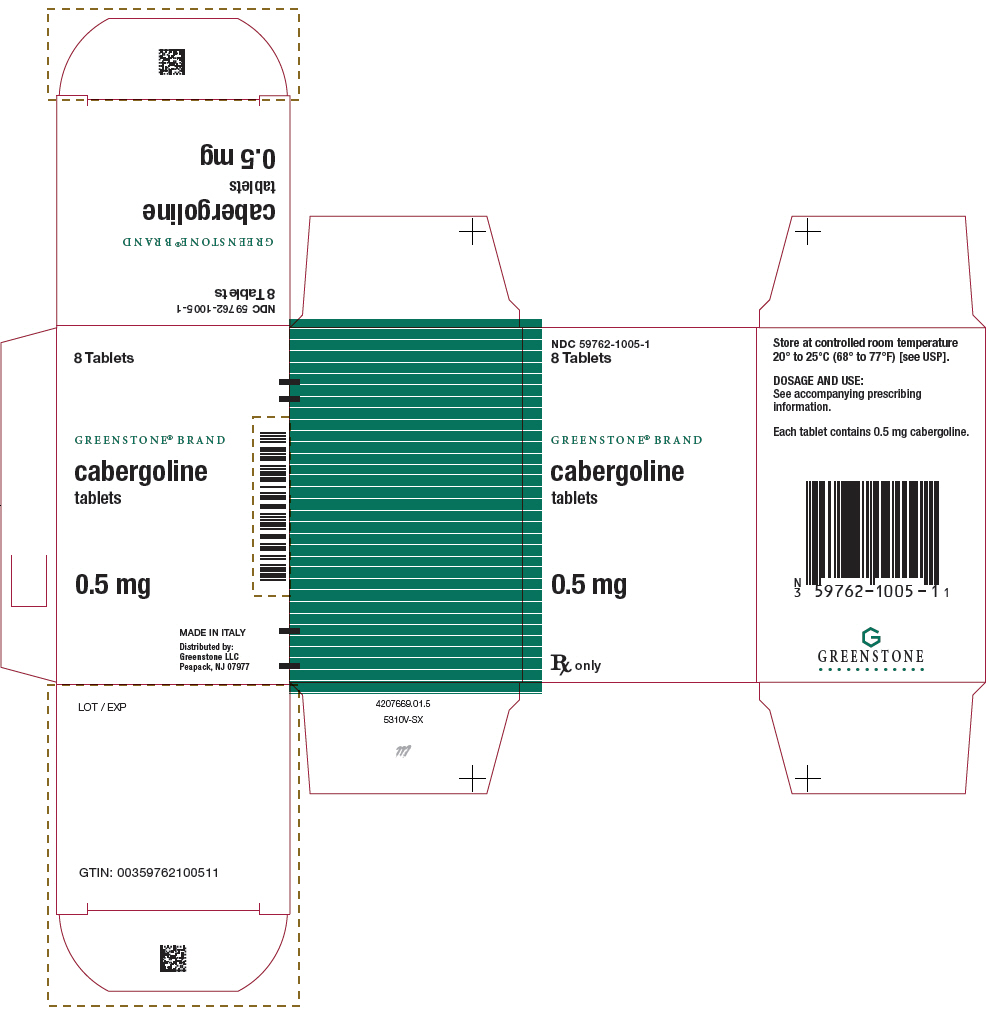 DRUG LABEL: Cabergoline
NDC: 59762-1005 | Form: TABLET
Manufacturer: Mylan Pharmaceuticals Inc.
Category: prescription | Type: HUMAN PRESCRIPTION DRUG LABEL
Date: 20250930

ACTIVE INGREDIENTS: CABERGOLINE 0.5 mg/1 1
INACTIVE INGREDIENTS: LEUCINE; LACTOSE, UNSPECIFIED FORM

HIGHLIGHTS OF PRESCRIBING INFORMATION

These highlights do not include all the information needed to use CABERGOLINE safely and effectively. See full prescribing information for CABERGOLINE.
CABERGOLINE tablets, for oral use
Initial U.S. Approval: 1996

RECENT MAJOR CHANGES

Indications and Usage (1) | 4/2025
Warnings and Precautions, Cardiac Valvulopathy and Pericardial Fibrosis (5.1) | 4/2025
Warnings and Precautions, Risks with Use of CABERGOLINE for Postpartum Lactation Inhibition or Suppression (5.4) | 4/2025

1 INDICATIONS AND USAGE

CABERGOLINE is an ergot derivative indicated for the treatment of hyperprolactinemic disorders, either idiopathic or due to pituitary adenomas in adults. (1)
Limitations of Use
Avoid use of CABERGOLINE for the inhibition or suppression of postpartum physiologic lactation because of the risk of serious adverse reactions. (5.4)

2 DOSAGE AND ADMINISTRATION

- Before initiating CABERGOLINE evaluate for valvular heart disease, including with an echocardiogram. If valvular disease is detected, do not administer CABERGOLINE. (2.1)
- Recommended starting dosage of CABERGOLINE is 0.25 mg orally twice weekly. (2.2)
- Titrate CABERGOLINE to achieve normal serum prolactin levels by increasing CABERGOLINE by 0.25 mg orally twice weekly at intervals of no less than 4 weeks. (2.2)
- Maximum recommended dosage is 1 mg orally, twice weekly. (2.2)

3 DOSAGE FORMS AND STRENGTHS

Tablets: 0.5 mg, white, with functional score. (3)

4 CONTRAINDICATIONS

- Uncontrolled hypertension. (4)
- Known hypersensitivity to ergot derivatives. (4)
- History of cardiac valvular disorders, or pericardial fibrosis. (5.1)
- History of pleural, pulmonary, or retroperitoneal fibrotic disorders. (5.2)

5 WARNINGS AND PRECAUTIONS

- Cardiac Valvulopathy and Pericardial Fibrosis: Before initiating CABERGOLINE, perform a cardiovascular evaluation, including echocardiogram, to evaluate for valvular disease. During CABERGOLINE treatment, monitor for the development of valvulopathy with a cardiac echocardiogram at intervals of 6 to 12 months or as clinically indicated and monitor for chest pain and signs and symptoms of heart failure (if heart failure occurs, exclude valvular fibrosis and pericarditis). Consider additional clinical and diagnostic monitoring at baseline and as necessary during CABERGOLINE treatment. Use CABERGOLINE in patients treated with other drugs associated with valvulopathy only if the potential benefit of CABERGOLINE outweighs the risk. Discontinue CABERGOLINE if the patient has a new diagnosis of valvular regurgitation, valvular restriction, valve leaflet thickening, or pericarditis. (5.1)
- Pleural, Pulmonary and Retroperitoneal Fibrosis: During CABERGOLINE treatment monitor for signs and symptoms of progressive fibrosis, (e.g., pleuro-pulmonary disease, renal impairment, ureteral/abdominal vascular obstruction). Consider clinical and diagnostic monitoring for pleural, pulmonary, and retroperitoneal fibrosis at baseline and as necessary during CABERGOLINE treatment. If pleural, pericardial, retroperitoneal, or pulmonary fibrosis occur, discontinue CABERGOLINE. (5.2)
- Orthostatic Hypotension: Check blood pressure at baseline and during treatment with CABERGOLINE and monitor for orthostatic hypotension. (5.3)
- Risks with Use of CABERGOLINE for Postpartum Lactation Inhibition or Suppression: Avoid use of CABERGOLINE for the inhibition or suppression of physiologic lactation. Use of bromocriptine, another dopamine agonist for this unapproved use has been associated with cases of hypertension, stroke, myocardial infarction, seizures, and death. (5.4)
- Impulse Control Disorders and Compulsive Behaviors: Specifically ask patients about the development of new or increased gambling urges, sexual urges, uncontrolled spending, or other urges while being treated with CABERGOLINE. Consider dosage reduction or stopping CABERGOLINE if a patient develops such urges while taking CABERGOLINE. (5.5)

6 ADVERSE REACTIONS

The most common adverse reactions (incidence >10%) are nausea, headache, and dizziness. (6)
To report SUSPECTED ADVERSE REACTIONS, contact Greenstone LLC at 1-877-446-3679 or FDA at 1-800-FDA-1088 or www.fda.gov/medwatch.

7 DRUG INTERACTIONS

CABERGOLINE, a dopamine receptor agonist, is not recommended for concomitant use with D2-antagonists, such as phenothiazines, butyrophenones, thioxanthenes, or metoclopramide. (7)

8 USE IN SPECIFIC POPULATIONS

Pregnancy: If conception occurs during CABERGOLINE therapy, discontinue CABERGOLINE if the risks to the mother or fetus outweigh the benefits to the mother. (8.1)

FULL PRESCRIBING INFORMATION

1 INDICATIONS AND USAGE

CABERGOLINE is an ergot derivative indicated for the treatment of hyperprolactinemic disorders, either idiopathic or due to pituitary adenomas in adults.

Limitations of Use

Avoid use of CABERGOLINE for the inhibition or suppression of postpartum physiologic lactation because of the risk of serious adverse reactions [see Warnings and Precautions (5.4)].

2 DOSAGE AND ADMINISTRATION

2.1 Recommended Evaluation Before Initiating CABERGOLINE

Before initiating CABERGOLINE evaluate for valvular heart disease, including with an echocardiogram. If valvular disease is detected, do not administer CABERGOLINE [see Contraindications (4) and Warnings and Precautions (5.1)].

2.2 Recommended Dosage

The recommended starting dosage of CABERGOLINE is 0.25 mg orally twice weekly. Titrate CABERGOLINE to achieve normal serum prolactin levels by increasing CABERGOLINE by 0.25 mg orally twice weekly at intervals of no less than 4 weeks. The maximum recommended dosage is 1 mg orally, twice weekly [see Warnings and Precautions (5.2)]. Administer CABERGOLINE with or without food [see Clinical Pharmacology (12.3)].

If CABERGOLINE is discontinued, monitor the serum prolactin level periodically to determine whether CABERGOLINE should be reinstituted.

3 DOSAGE FORMS AND STRENGTHS

Tablets: 0.5 mg, white, with functional score, oblong scored on one side with the letter P and the letter U on either side of the breakline, engraved with the number 700 on the opposite side.

4 CONTRAINDICATIONS

CABERGOLINE is contraindicated in patients with:

- Uncontrolled hypertension.
- Known hypersensitivity to ergot derivatives.
- History of cardiac valvular disorders, as suggested by anatomical evidence of valvulopathy of any valve, determined by pre-treatment evaluation including echocardiographic demonstration of valve leaflet thickening, valve restriction, or mixed valve restriction-stenosis, or history of pericardial fibrosis [see Warnings and Precautions (5.1)].
- History of pleural, pulmonary, or retroperitoneal fibrotic disorders [see Warnings and Precautions (5.2)].

5 WARNINGS AND PRECAUTIONS

5.1 Cardiac Valvulopathy and Pericardial Fibrosis

Before initiating CABERGOLINE, perform a cardiovascular evaluation, including with an echocardiogram, to evaluate for valvular disease. CABERGOLINE is contraindicated in the presence of valvular disease or pericardial fibrosis [see Contraindications (4)].

Cases of valvular and pericardial fibrosis have often manifested as heart failure. Following CABERGOLINE treatment initiation, monitor for the development of valvulopathy with a cardiac echocardiogram at intervals of 6 to 12 months or as clinically indicated with new onset edema, cardiac murmur, dyspnea, or heart failure. During CABERGOLINE treatment, monitor for chest pain and signs and symptoms of heart failure and if heart failure occurs, valvular fibrosis and pericarditis should be excluded. Consider clinical and diagnostic monitoring such as erythrocyte sedimentation rate, serum creatinine measurements, chest-x- ray, and other investigations and cardiac imaging at baseline and as necessary while patients are treated with during CABERGOLINE treatment. Use CABERGOLINE in patients treated with other drugs associated with valvulopathy only if the potential benefit of CABERGOLINE outweighs the risk.

Discontinue CABERGOLINE if the patient has a new diagnosis of valvular regurgitation, valvular restriction, valve leaflet thickening, or pericarditis.

Postmarketing cases of cardiac valvulopathy have been reported in patients who received CABERGOLINE. These cases have generally occurred during administration of high doses of CABERGOLINE (>2 mg/day) for the treatment of Parkinson’s disease (PD) (CABERGOLINE is not approved for the treatment of PD). Cases of cardiac valvulopathy have also been reported in patients who received lower dosages of CABERGOLINE for the treatment of hyperprolactinemic disorders. In a 12-year, multi-country retrospective cohort study, the use of CABERGOLINE for PD was associated with an increased risk of cardiac valvular regurgitation (CVR). Compared to non-ergot-derived dopamine agonists and levodopa, CVR with CABERGOLINE use had an incidence rate per 10,000 person years of 68 (95% CI: 37, 115) versus 10 (95% CI: 5, 19) for non-ergot dopamine agonists and 11 (95% CI: 7, 17) for levodopa.

5.2 Pleural, Pulmonary and Retroperitoneal Fibrosis

CABERGOLINE is contraindicated in patients with a history of pleural, pulmonary, or retroperitoneal fibrosis. During CABERGOLINE treatment monitor for signs and symptoms of progressive fibrosis, including:

- Pleuro-pulmonary disease (e.g., dyspnea, shortness of breath, persistent cough, chest pain).
- Renal impairment or ureteral/abdominal vascular obstruction (e.g., pain in the loin/flank, lower limb edema, abdominal masses or tenderness that may indicate retroperitoneal fibrosis).

Consider clinical and diagnostic monitoring for pleural, pulmonary, and retroperitoneal fibrosis such as with erythrocyte sedimentation rate, serum creatinine measurements, chest-x-ray, and other investigations at baseline and as necessary during CABERGOLINE treatment. If pleural, pericardial, retroperitoneal, or pulmonary fibrosis occur, discontinue CABERGOLINE.

Postmarketing cases of pleural, pulmonary, and retroperitoneal fibrosis have been reported following CABERGOLINE administration. Some reports were in patients previously treated with other ergotinic dopamine agonists. CABERGOLINE-treated patients who developed a pleural effusion or pulmonary fibrosis and subsequently discontinued CABERGOLINE had improvement of their pulmonary symptoms.

5.3 Orthostatic Hypotension

Check blood pressure at baseline and during treatment with CABERGOLINE and monitor for orthostatic hypotension. Warn patients about the risk of orthostatic hypotension and precautions to take when rising from a supine or sitting position. Instruct patients to report dizziness or lightheadedness with changes in position to their healthcare provider.

CABERGOLINE can cause orthostatic hypotension [see Adverse Reactions (6.1)]. In a 4-week, placebo-controlled trial in patients with hyperprolactinemic disorders, the percentage of CABERGOLINE-treated patients and placebo-treated patients who developed orthostatic hypotension was 4% and 0%, respectively [see Adverse Reactions (6.1)]. The risk of orthostatic hypotension is greater in CABERGOLINE-treated patients when taking concomitant drugs that lower blood pressure.

5.4 Risks with Use of CABERGOLINE for Postpartum Lactation Inhibition or Suppression

Avoid use of CABERGOLINE for the inhibition or suppression of postpartum physiologic lactation because of the risk of serious adverse reactions. Use of bromocriptine, another dopamine agonist for this unapproved use has been associated with cases of hypertension, stroke, myocardial infarction seizures, and death.

5.5 Impulse Control Disorders and Compulsive Behaviors

Because patients may not recognize impulse control and compulsive behaviors as abnormal, it is important for health care providers to specifically ask patients about the development of new or increased gambling urges, sexual urges, uncontrolled spending, or other urges while being treated with CABERGOLINE. Consider dosage reduction or stopping CABERGOLINE if a patient develops such urges while taking CABERGOLINE.

Patients can experience intense urges to gamble or to spend money, increased sexual urges, binge eating, and/or other intense urges, and the inability to control these urges while taking one or more drugs that increase central dopaminergic tone, including CABERGOLINE. In some cases, these urges were reported to have stopped when the dosage was reduced, or the drug was stopped.

6 ADVERSE REACTIONS

The following clinically significant adverse reactions are described elsewhere in the labeling:

- Cardiac Valvulopathy and Pericardial Fibrosis [see Warnings and Precautions (5.1)].
- Pleural, Retroperitoneal, and Pulmonary Fibrosis [see Warnings and Precautions (5.2)].
- Orthostatic Hypotension [see Warnings and Precautions (5.3)].
- Impulse Control Disorders and Compulsive Behaviors [see Warnings and Precautions (5.5)].

6.1 Clinical Trials Experience

Because clinical trials are conducted under widely varying conditions, adverse reaction rates observed in the clinical trials of a drug cannot be directly compared to rates in the clinical trials of another drug and may not reflect the rates observed in practice.

The safety of CABERGOLINE has been evaluated in more than 900 patients with hyperprolactinemic disorders. In a 4-week, double-blind, placebo-controlled trial (CABERGOLINE vs. placebo) [see Clinical Studies (14)], the incidence of the most common adverse reactions during the placebo-controlled trial in patients with hyperprolactinemic disorders is presented in Table 1.

Table 1. Adverse Reactions (n (%)) [Adverse reactions that occurred ≥1% in the CABERGOLINE group and frequency more than that reported in the placebo group.] During the 4-Week, Double-Blind, Placebo-Controlled Trial in Hyperprolactinemic Females
 | CABERGOLINE; (n=168) | Placebo; (n=20)
Nausea | 45 (27%) | 4 (20%)
Headache | 43 (26%) | 5 (25%)
Dizziness | 25 (15%) | 1 (5%)
Constipation | 16 (10%) | 0%
Fatigue | 12 (7%) | 0%
Postural hypotension | 6 (4%) | 0%
Dyspepsia | 4 (2%) | 0%
Vomiting | 4 (2%) | 0%
Nervousness | 4 (2%) | 0%
Vertigo | 2 (1%) | 0%
Paresthesia | 2 (1%) | 0%
Breast pain | 2 (1%) | 0%
Dysmenorrhea | 2 (1%) | 0%
Abnormal vision | 2 (1%) | 0%

In the 8-week, double-blind period of the comparative trial with bromocriptine, 2% (4/221) of CABERGOLINE-treated patients (0.5 mg twice weekly) discontinued treatment because of an adverse event and 6% (14/231) of bromocriptine-treated patients (at a dose of 2.5 mg twice daily) discontinued treatment because of an adverse event. The most common reasons for CABERGOLINE discontinuation were headache, nausea, and vomiting (3, 2, and 2 patients, respectively). The incidence of the most common adverse events during the double-blind period of the comparative trial with bromocriptine is presented in Table 2.

Table 2. Adverse Events [Adverse events reported ≥1% in the CABERGOLINE group. Abbreviation: n=number of patients.] During the 8-Week, Double-Blind Period of the Comparative Trial in Hyperprolactinemic Females
 | CABERGOLINE; (n=221) | Bromocriptine; (n=231)
Nausea | 63 (29%) | 100 (43%)
Headache | 58 (26%) | 62 (27%)
Dizziness | 38 (17%) | 42 (18%)
Constipation | 15 (7%) | 21 (9%)
Asthenia | 13 (6%) | 15 (6%)
Abdominal pain | 12 (5%) | 19 (8%)
Dyspepsia | 11 (5%) | 16 (7%)
Fatigue | 10 (5%) | 18 (8%)
Vertigo | 9 (4%) | 10 (4%)
Vomiting | 9 (4%) | 16 (7%)
Depression | 7 (3%) | 5 (2%)
Hot flashes | 6 (3%) | 3 (1%)
Breast pain | 5 (2%) | 8 (3%)
Dry mouth | 5 (2%) | 2 (1%)
Paresthesia | 5 (2%) | 6 (3%)
Somnolence | 5 (2%) | 5 (2%)
Diarrhea | 4 (2%) | 7 (3%)
Flatulence | 4 (2%) | 3 (1%)
Pain | 4 (2%) | 6 (3%)
Acne | 3 (1%) | 0%
Anorexia | 3 (1%) | 3 (1%)
Anxiety | 3 (1%) | 3 (1%)
Hypotension | 3 (1%) | 4 (2%)
Insomnia | 3 (1%) | 2 (1%)
Syncope | 3 (1%) | 3 (1%)
Abnormal vision | 2 (1%) | 2 (1%)
Arthralgia | 2 (1%) | 0%
Dependent edema | 2 (1%) | 1 (<1%)
Dysmenorrhea | 2 (1%) | 1 (<1%)
Impaired concentration | 2 (1%) | 1 (<1%)
Influenza-like symptoms | 2 (1%) | 0%
Malaise | 2 (1%) | 0%
Nervousness | 2 (1%) | 5 (2%)
Palpitation | 2 (1%) | 5 (2%)
Periorbital edema | 2 (1%) | 2 (1%)
Peripheral edema | 2 (1%) | 1 (<1%)
Pruritus | 2 (1%) | 1 (<1%)
Rhinitis | 2 (1%) | 9 (4%)
Throat irritation | 2 (1%) | 0%
Toothache | 2 (1%) | 0%

Events that were reported at an incidence of <1% in the clinical studies follow:

- Body As a Whole: facial edema, influenza-like symptoms, malaise
- Cardiovascular System: hypotension, syncope, palpitations
- Digestive System: dry mouth, flatulence, diarrhea, anorexia
- Metabolic and Nutritional System: weight loss, weight gain
- Nervous System: somnolence, nervousness, paresthesia, insomnia, anxiety
- Respiratory System: nasal stuffiness, epistaxis
- Skin and Appendages: acne, pruritus
- Special Senses: abnormal vision
- Urogenital System: dysmenorrhea, increased libido

6.2 Postmarketing Experience

The following adverse reactions have been identified during post-approval use of CABERGOLINE. Because these reactions are reported voluntarily from a population of uncertain size, it is not always possible to reliably estimate their frequency or establish a causal relationship to drug exposure.

- Psychiatric: impulse control disorders and compulsive behaviors including, hypersexuality, increased libido, pathological gambling; psychotic disorder, aggression
- Skin and subcutaneous: alopecia

7 DRUG INTERACTIONS

CABERGOLINE, a dopamine receptor agonist, is not recommended for concomitant use with D2-antagonists, such as phenothiazines, butyrophenones, thioxanthenes, or metoclopramide.

8 USE IN SPECIFIC POPULATIONS

8.1 Pregnancy

Risk Summary

If conception occurs during CABERGOLINE therapy, discontinue CABERGOLINE if the risks to the mother or fetus outweigh the benefits to the mother. There are risks to the mother associated with the use of CABERGOLINE (see Clinical Considerations).

The estimated background risk of major birth defects and miscarriage in patients with hyperprolactinemic disorders, either idiopathic or due to pituitary adenomas is unknown. All pregnancies have a risk of birth defect, loss, or other adverse outcomes. In the U.S. general population, the estimated background risk of major birth defects and miscarriage in clinically recognized pregnancies is 2% to 4% and 15% to 20%, respectively.

Clinical Considerations

Maternal Adverse Reactions: In general, avoid use of dopamine agonists, including CABERGOLINE, during pregnancy and the postpartum period. The risks of CABERGOLINE use increase in pregnant females with pregnancy-induced hypertension, preeclampsia, and eclampsia.

Data

Human Data: Published case reports have not reported a clear association with CABERGOLINE and major birth defects, miscarriage, or adverse fetal outcomes when CABERGOLINE was used during early pregnancy. However, these case reports cannot definitely establish the absence of CABERGOLINE-associated risk.

Animal Data: Embryo-fetal development studies have been performed with cabergoline administered by oral gavage in mice, rats, and rabbits:

- There were no teratogenic effects in the presence of maternal toxicity in mice given cabergoline at doses up to 8 mg/kg/day (approximately 55 times the maximum recommended human dose based on body surface area) during the period of organogenesis.
- A dose of 0.012 mg/kg/day (approximately 0.14 times the maximum recommended human dose) administered during the period of organogenesis in rats caused an increase in post-implantation loss. This finding is likely due to the role of prolactin in implantation in rats and is not thought to be relevant to humans.
- At doses of 0.5 mg/kg/day (approximately 19 times the maximum recommended human dose) administered during the period of organogenesis in rabbits, cabergoline caused maternal toxicity characterized by a loss of body weight and decreased food consumption. Doses of 4 mg/kg/day (approximately 150 times the maximum recommended human dose) administered during the period of organogenesis in the rabbit caused an increased occurrence of various malformations. However, in another study in rabbits, no treatment-related malformations or embryofetal toxicity were observed at doses up to 8 mg/kg/day (approximately 300 times the maximum recommended human dose).

8.2 Lactation

Risk Summary

CABERGOLINE is not recommended in postpartum women who are breastfeeding or who are planning to breastfeed. Avoid use of CABERGOLINE for the inhibition or suppression of physiologic lactation [see Indications and Usage (1) and Warnings and Precautions (5.4)].

8.4 Pediatric Use

Safety and effectiveness of CABERGOLINE in pediatric patients have not been established.

8.5 Geriatric Use

Clinical studies of CABERGOLINE did not include sufficient numbers of patients 65 years of age and older to determine whether they respond differently from younger adult patients.

8.6 Hepatic Impairment

The use of CABERGOLINE in patients with severe hepatic impairment (HI) (Child-Pugh C) is not recommended. When using CABERGOLINE in patients with moderate HI (Child-Pugh B) increase monitoring of CABERGOLINE-associated adverse reactions. The recommendations for use of CABERGOLINE in patients with mild HI (Child Pugh A) is the same as those with normal hepatic function.

Patients with moderate or severe HI had increased cabergoline exposure [see Clinical Pharmacology (12.3)], which may increase the risk of CABERGOLINE-associated adverse reactions.

10 OVERDOSAGE

Take measures to support blood pressure, if necessary. Consider contacting the Poison Help line (1-800-222-1222) or a medical toxicologist for additional overdose management recommendations.

11 DESCRIPTION

Cabergoline is an ergot derivative and dopamine receptor agonist. The chemical name for cabergoline is 1-[(6-allylergolin-8ß-yl)-carbonyl]-1-[3-(dimethylamino) propyl]-3-ethylurea. Its empirical formula is C26H37N5O2, and its molecular weight is 451.62. The structural formula is as follows

Cabergoline is a white powder soluble in ethyl alcohol, chloroform, and N, N-dimethylformamide (DMF); slightly soluble in 0.1N hydrochloric acid; very slightly soluble in n-hexane; and insoluble in water.

CABERGOLINE tablets, for oral administration, contain 0.5 mg of cabergoline and the inactive ingredients of leucine, USP, and lactose, NF.

12 CLINICAL PHARMACOLOGY

12.1 Mechanism of Action

Cabergoline is an ergot derivative and dopamine receptor agonist with a high affinity for D2 receptors. Results of in vitro studies demonstrate that cabergoline exerts a direct inhibitory effect on the secretion of prolactin by rat pituitary lactotrophs. Cabergoline decreased serum prolactin levels in reserpinized rats. Receptor-binding studies indicate that cabergoline has low affinity for dopamine D1, α1- and α2-adrenergic, and 5-HT1- and 5-HT2-serotonin receptors.

12.2 Pharmacodynamics

The exposure-response relationship and time course of pharmacodynamic response for the safety and effectiveness of CABERGOLINE have not been fully characterized.

12.3 Pharmacokinetics

Absorption

The time to reach maximum cabergoline plasma concentration was 2 to 3 hours after single oral doses of 0.5 mg to 1.5 mg (1.5 times the maximum recommended dose) of CABERGOLINE in healthy subjects. Following dosing of CABERGOLINE between 0.5 mg to 7 mg (7 times the maximum recommended dose), cabergoline plasma levels appeared to be dose-proportional. The absolute bioavailability of cabergoline is unknown. A significant fraction of the administered dose undergoes a first-pass effect.

Effect of Food: High-fat food did not alter the pharmacokinetics of cabergoline [see Dosage and Administration (2.2)].

Distribution

Protein binding of cabergoline was 40% to 42%.

Elimination

The elimination half-life of cabergoline estimated from urinary data of 12 healthy subjects ranged between 63 to 69 hours.

Metabolism: Cabergoline is extensively metabolized, predominately via hydrolysis of the acylurea bond or the urea moiety. Hydrolysis of the acylurea or urea moiety abolishes the prolactin-lowering effect of cabergoline, and major metabolites identified thus far do not contribute to the therapeutic effect.

Excretion: After oral dosing of radioactive cabergoline to 5 healthy volunteers, approximately 22% and 60% of the dose was excreted within 20 days in the urine and feces, respectively. Less than 4% of the dose was excreted unchanged in the urine. Nonrenal and renal clearances for cabergoline are about 3.2 L/min and 0.08 L/min, respectively. Urinary excretion in hyperprolactinemic patients was similar.

Specific Populations

Patients with Hepatic Impairment:

In a pharmacokinetic hepatic impairment (HI) study [see Use in Specific Populations (8.6)]:

- In 4 CABERGOLINE-treated patients with mild HI (Child-Pugh A), no effect on mean area under the cabergoline plasma concentration-time curve (AUC) was observed.
- In 4 CABERGOLINE-treated patients with moderate HI (Child-Pugh B) there was a 1.5-fold increase in mean cabergoline AUC.
- In 4 CABERGOLINE-treated patients with severe HI (Child-Pugh C) there was a 5.6-fold increase in the mean cabergoline AUC.

Male and Female Patients: Males aged 20 to 34 years were shown to have had higher Cmax than females aged 20 to 27 years) while males aged 66 to 75 years had lower Cmax compared to females aged 66 to 74 years. The clinical significance of the findings is unknown.

Patients with Renal Impairment: The pharmacokinetics of cabergoline were not altered in 12 patients with moderate-to-severe renal impairment as assessed by creatinine clearance.

13 NONCLINICAL TOXICOLOGY

13.1 Carcinogenesis, Mutagenesis, Impairment of Fertility

Carcinogenesis

Carcinogenicity studies were conducted in mice and rats with cabergoline given by gavage at doses up to 0.98 mg/kg/day and 0.32 mg/kg/day, respectively. These doses are 7 times and 4 times the maximum recommended human dose calculated on a body surface area basis using total mg/m^2/week in rodents and mg/m^2/week for a 50 kg human.

There was a slight increase in the incidence of cervical and uterine leiomyomas and uterine leiomyosarcomas in mice. In rats, there was a slight increase in malignant tumors of the cervix and uterus and interstitial cell adenomas. The occurrence of tumors in female rodents may be related to the prolonged suppression of prolactin secretion because prolactin is needed in rodents for the maintenance of the corpus luteum. In the absence of prolactin, the estrogen/progesterone ratio is increased, thereby increasing the risk for uterine tumors. In male rodents, the decrease in serum prolactin levels was associated with an increase in serum luteinizing hormone, which is thought to be a compensatory effect to maintain testicular steroid synthesis. Since these hormonal mechanisms are thought to be species-specific, the relevance of these tumors to humans is not known.

Mutagenesis

The mutagenic potential of cabergoline was evaluated and found to be negative in a battery of in vitro tests. These tests included the bacterial mutation (Ames) test with Salmonella typhimurium, the gene mutation assay with Schizosaccharomyces pombe P1 and V79 Chinese hamster cells, DNA damage and repair in Saccharomyces cerevisiae D4, and chromosomal aberrations in human lymphocytes. Cabergoline was also negative in the bone marrow micronucleus test in the mouse.

Impairment of Fertility

In female rats, a daily cabergoline dose of 0.003 mg/kg for 2 weeks prior to mating and throughout the mating period inhibited conception. This dose represents approximately 0.04 times the maximum recommended human dose calculated on a body surface area basis using total mg/m^2/week in rats and mg/m^2/week for a 50 kg human. This finding is likely due to the role of prolactin in implantation in rats and is not thought to be relevant to humans.

14 CLINICAL STUDIES

The prolactin-lowering efficacy of CABERGOLINE was demonstrated in 647 females with hyperprolactinemic disorders (including 55% microprolactinomas, 7% macroprolactinomas, 3% empty sella syndromes, and 3% idiopathic) in two randomized, double-blind, studies: one 4-week placebo-controlled dose-response study with an 12-month open-label extension (Study 1) and one 8-week active comparator study comparing CABERGOLINE and bromocriptine with 16-week open extension (Study 2).

Study 1: 4-Week Placebo-Controlled Dose-Response Study

Study 1 enrolled 188 non-pregnant, hyperprolactinemic females (these patients had a prolactin level >20 ng/ml (the upper normal reference limit)) with the following hyperprolactinemic etiologies: macroprolactinoma (60%, n=113), idiopathic (36%, n=67) and another etiology (4%, n=8). Patients had a mean age of 32 years (range, 16-46 years of age), 99% were White (n=186), 0.5% were Asian (n=1) and 0.5% were another race (n=1). Patients were randomized one of the following five oral treatments given twice weekly for four weeks (for the CABERGOLINE groups, the first week the CABERGOLINE dosage was lower to reduce the risk of hypotensive reactions):

- Group 1: placebo twice weekly (n=20),
- Group 2: 0.0625 mg of CABERGOLINE twice weekly for the first week followed by 0.125 mg twice weekly for the next three weeks (n=42)-this dosage is not recommended because this dosage was not effective and results from this group are not presented below [see Dosage and Administration (2.2)],
- Group 3: 0.25 mg of CABERGOLINE twice weekly for the first week followed 0.5 mg twice weekly for the next three weeks (n=42),
- Group 4: 0.375 mg of CABERGOLINE twice weekly for the first week followed 0.75 mg twice weekly for the next three weeks (n=42), and
- Group 5: 0.5 mg of CABERGOLINE twice weekly for the first week followed 1 mg twice weekly for the next three weeks 0.75 mg, (n=42).

In Study 1, the endpoint was the percentage of patients who achieved a normal serum prolactin level (<20 ng/dL) at the end of the 4-week treatment period. At 4-weeks, 0%, 76%, 74% and 95% of patients in the placebo group (group 1), group 3, group 4, and group 5, achieved normal serum prolactin levels, respectively (p <0.0001 across all the CABERGOLINE groups vs. placebo).

Study 2: 8-Week Active Comparator Study

Study 2 was an 8-week, randomized, double-blind active-control study that compared CABERGOLINE (n=223) with bromocriptine (n=236) for the treatment of hyperprolactinemic amenorrhea. In this study, patients had a mean age of 31 years (range 16 – 46 years of age). Patients were randomized to oral CABERGOLINE 0.5 mg twice weekly or oral bromocriptine 2.5 mg twice daily for eight weeks (there was an attrition rate respectively of 46% and 43%, in the CABERGOLINE and bromocriptine groups, respectively). Endpoints included percentage of patients who achieved the following at 8 weeks:

- A normal serum prolactin level (<20 ng/dL)
- Restoration of menses
- Disappearance of galactorrhea

In Study 2, at 8 weeks, CABERGOLINE-treated and bromocriptine-treated patients had a normal serum prolactin level (77% and 59%, respectively), restoration of menses (77% and 70% respectively), and disappearance of galactorrhea, (73% and 56%, respectively).

The durability of the efficacy of CABERGOLINE beyond 24 months of therapy has not been established.

16 HOW SUPPLIED/STORAGE AND HANDLING

CABERGOLINE tablets are white, scored, oblong, with functional score on one side with the letter P and the letter U on either side of the breakline, engraved with the number 700 on the opposite side and they are available in the following configuration: 0.5 mg strength, 8-count bottle, and NDC number 59762-1005-1.

Store at controlled room temperature 20°C to 25°C (68°F to 77°F) [see USP]. Store the tablets in the original container.

17 PATIENT COUNSELING INFORMATION

Advise the patient to read the FDA-approved patient labeling (Patient Information).

Fibrotic Conditions

There is a risk of cardiac valvulopathy, and pericardial, pleural, pulmonary, and retroperitoneal fibrosis with CABERGOLINE treatment. Advise patients to notify their healthcare provider if they develop shortness of breath, chest pain, persistent cough, difficulty with breathing when lying down, or swelling in their extremities [see Warnings and Precautions (5.1)].

Orthostatic Hypotension

Warn patients about the risk of orthostatic hypotension and instruct patients to rise slowly from a supine or sitting position. Advise patients to notify their healthcare provider if they develop dizziness or lightheadedness [see Warnings and Precautions (5.3)].

Impulse Control Disorders and Compulsive Behaviors

Patients should be alerted to the possibility that patients may experience intense urges to spend money uncontrollably, intense urges to gamble, increased sexual urges, and other intense urges and the inability to control these urges while taking CABERGOLINE. Advise patients to inform their health care provider if they develop new or increased uncontrolled spending, gambling urges, sexual urges, or other urges while being treated with CABERGOLINE [see Warnings and Precautions (5.5)].

Pregnancy

Advise patients to notify their health care provider if they suspect they are pregnant, become pregnant, or intend to become pregnant during therapy. A pregnancy test should be done if there is any suspicion of pregnancy and continuation of CABERGOLINE treatment should be discussed with their health care provider [see Use in Specific Populations (8.1)].

LAB-0304-10.0

PATIENT INFORMATION

CABERGOLINE (ka-BER-goe-leen)

(cabergoline) tablets

for oral use

What is CABERGOLINE?

CABERGOLINE is a prescription medicine used to treat a condition called hyperprolactinemia (increased levels of prolactin) in adults.

CABERGOLINE is not for use to prevent or suppress breastfeeding after having given birth (postpartum lactation).

It is not known if CABERGOLINE is safe and effective in children.

Who should not take CABERGOLINE?

Do not take CABERGOLINE if you:

- have uncontrolled high blood pressure.
- are allergic to medicines called ergot derivatives.
- have a history of heart valve disorders.
- have a history of fibrosis in your heart, chest, lungs or abdomen.

Before taking CABERGOLINE, tell your health care provider about all of your medical conditions, including if you:

- have heart problems.
- have low blood pressure.
- have liver problems.
- are pregnant or plan to become pregnant. It is not known if CABERGOLINE will harm your unborn baby. Tell your health care provider if you become pregnant or think you are pregnant during treatment with CABERGOLINE. A pregnancy test should be done if you think you may be pregnant. You and your health care provider should discuss whether to continue treatment with CABERGOLINE.
- are breastfeeding or plan to breastfeed. Talk to your health care provider about the best way to feed your baby if you take CABERGOLINE. Do not breastfeed during treatment while taking CABERGOLINE.
- Tell your health care provider about all the medicines you take, including prescription and over-the-counter medicines, vitamins, and herbal supplements. CABERGOLINE may affect the way other medicines work, and other medicines may affect the way CABERGOLINE works.

How should I take CABERGOLINE?

- Take CABERGOLINE exactly how your health care provider tells you to take it.
- Your health care provider should check for heart valve problems before starting treatment with CABERGOLINE.
- Take CABERGOLINE by mouth 2 times weekly or as directed by your health care provider.
- Take CABERGOLINE with or without food.
- Your health care provider should check your prolactin levels about every 4 weeks initially, and periodically thereafter, and may change your dose if needed.

If you take too much CABERGOLINE, call your Poison Help line at 1-800-222-1222 or go to the nearest hospital emergency room right away.

What are the possible side effects of CABERGOLINE?

CABERGOLINE can cause serious side effects, including:

- Heart valve problems and fibrosis (scarring). CABERGOLINE can cause heart valve problems and fibrosis in the heart, chest, lungs or areas of the stomach (abdomen). Call your health care provider right away if you get any of the following signs or symptoms of heart valve problems and fibrosis:
  - shortness of breath
  - chest pain
  - persistent cough
  - difficulty with breathing when lying down
  - swelling in the arms or legs
  - pain in the side (flank)
  - lump or tenderness in abdomen
- Decreased blood pressure (orthostatic hypotension). You may feel dizzy or lightheaded when you rise too quickly from a sitting or lying position. Talk to your health care provider if you have dizziness or lightheadedness.
- Unusual and uncontrollable (compulsive) urges. Some people taking CABERGOLINE have had unusual strong urges to gamble and gambling that cannot be controlled (compulsive gambling), and other compulsive urges including sexual urges, shopping, and eating or binge eating. Talk to your health care provider if you notice that you are having new or unusual strong urges or behaviors.

The most common side effects of CABERGOLINE include:

○ nausea

○ headache

○ dizziness

These are not all the possible side effects of CABERGOLINE. For more information, ask your health care provider including your pharmacist. Call your health care provider for medical advice about side effects. You may report side effects to FDA at 1-800-FDA-1088.

How should I store CABERGOLINE?

- Store CABERGOLINE at room temperature between (20°C to 25°C) 68°F to 77°F in the original container.

Keep CABERGOLINE and all medicines out of the reach of children.

General Information about the safe and effective use of CABERGOLINE.

Medicines are sometimes prescribed for purposes other than those listed in a Patient Information Leaflet. Do not use CABERGOLINE for a condition for which it was not prescribed. Do not give CABERGOLINE to other people, even if they have the same symptoms you have. It may harm them. You can ask your health care provider, including your pharmacist, for information that is written for health care providers.

What are the ingredients in CABERGOLINE?

Active ingredient: cabergoline.
Inactive ingredients: leucine, USP and lactose, NF.

For optional information, go to www.pfizer.com or call 1-800-438-1985.
LAB-1617-2.0

This Patient Information has been approved by the U.S. Food and Drug Administration Revised: 09/2025

PRINCIPAL DISPLAY PANEL - 8 Tablet Bottle Label

NDC 59762-1005-1
8 Tablets

GREENSTONE® BRAND

cabergoline
tablets

0.5 mg

Rx only

PRINCIPAL DISPLAY PANEL - 8 Tablet Bottle Carton

NDC 59762-1005-1
8 Tablets

GREENSTONE® BRAND

cabergoline
tablets

0.5 mg

Rx only